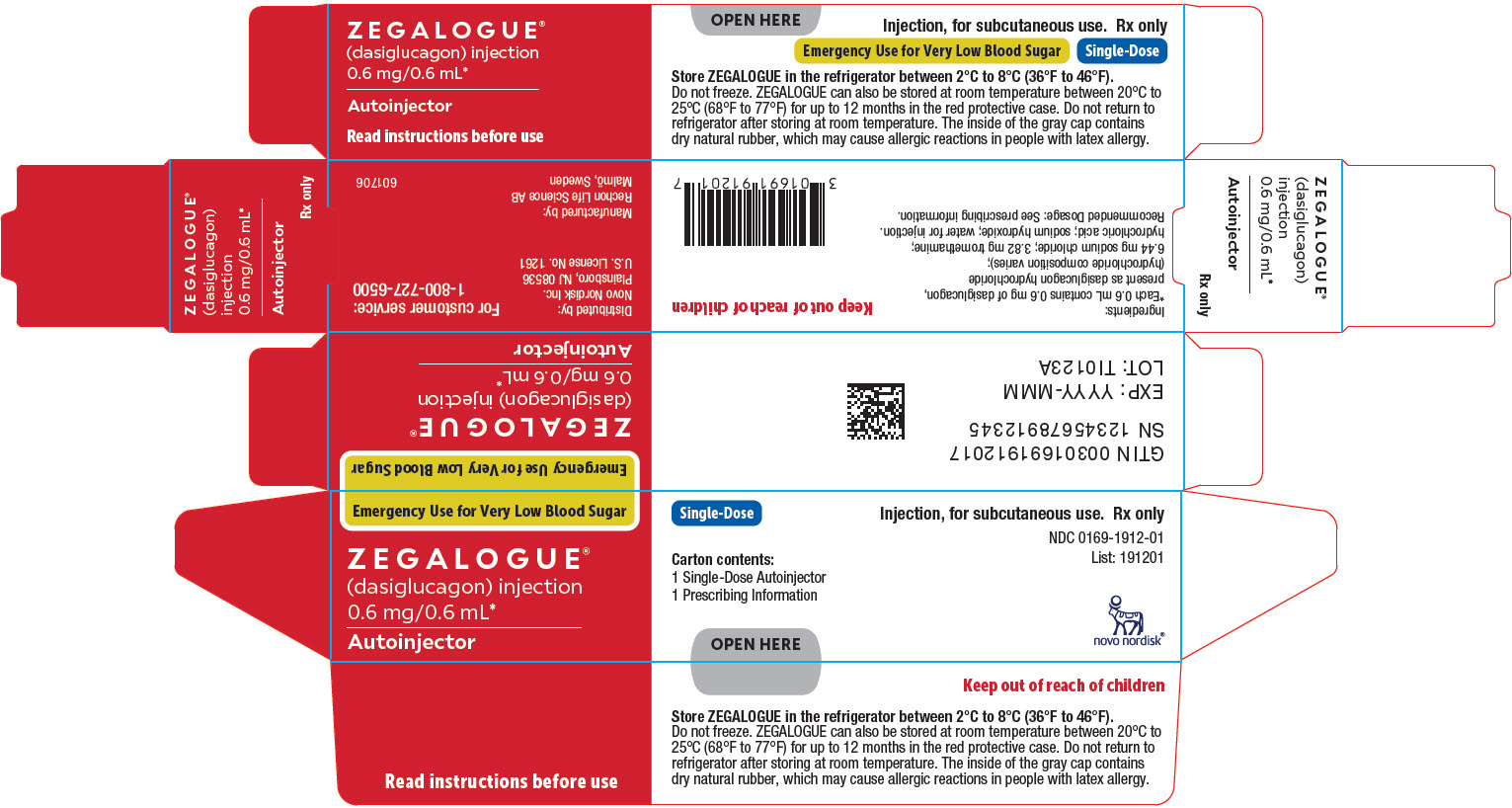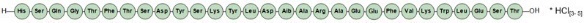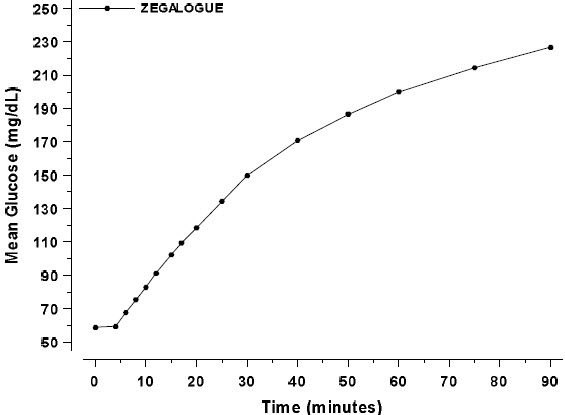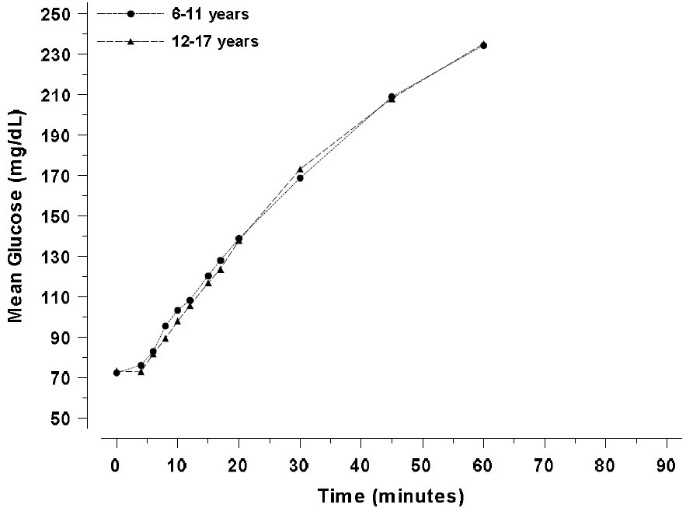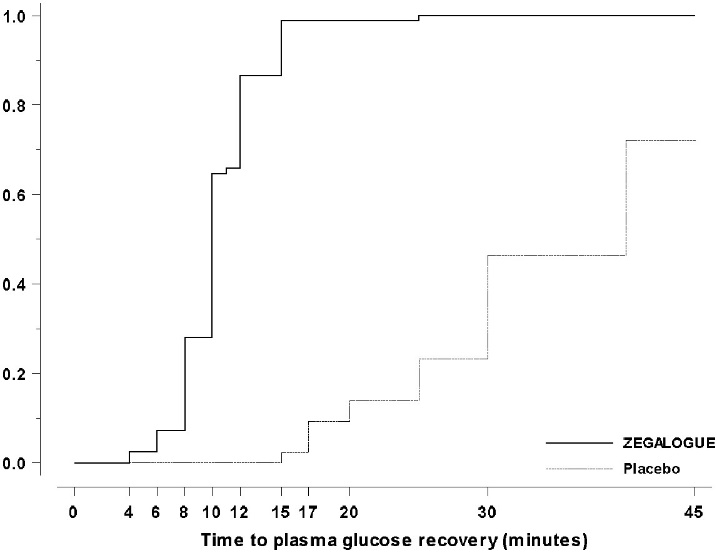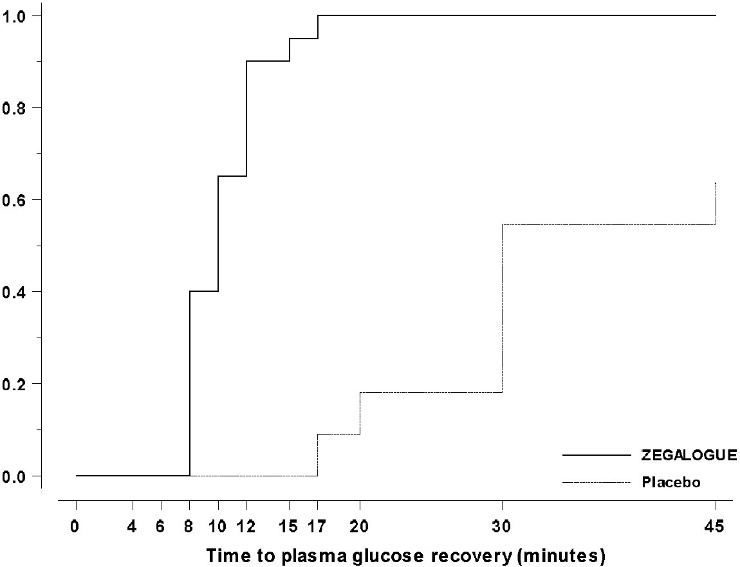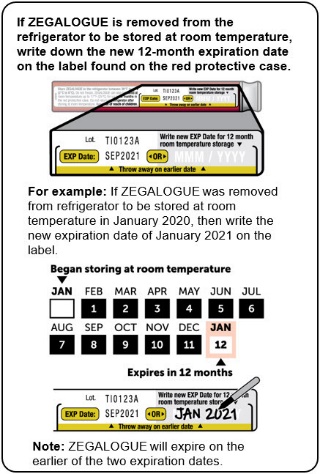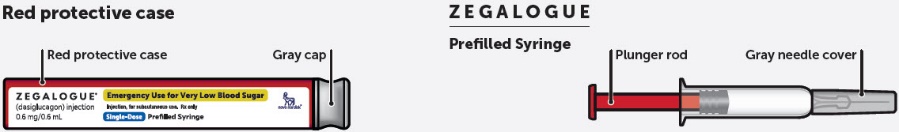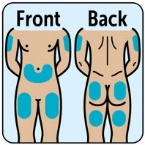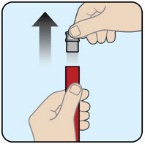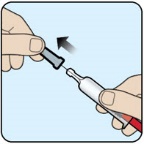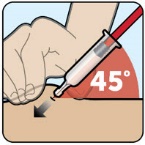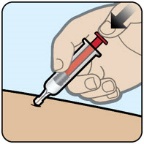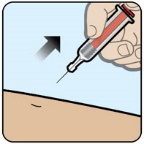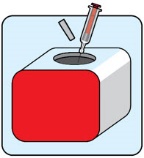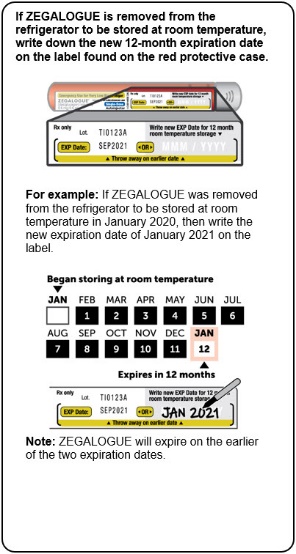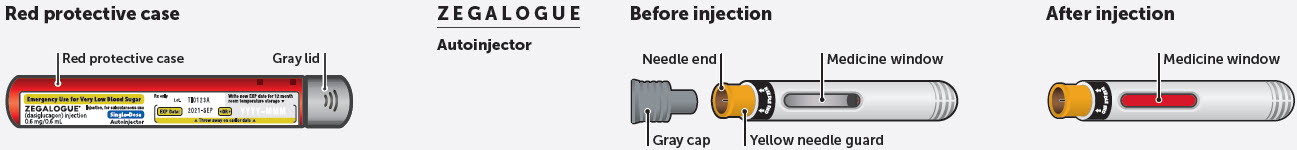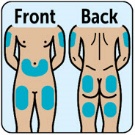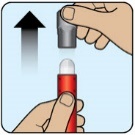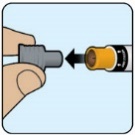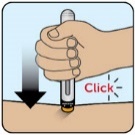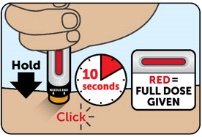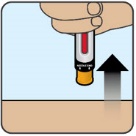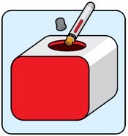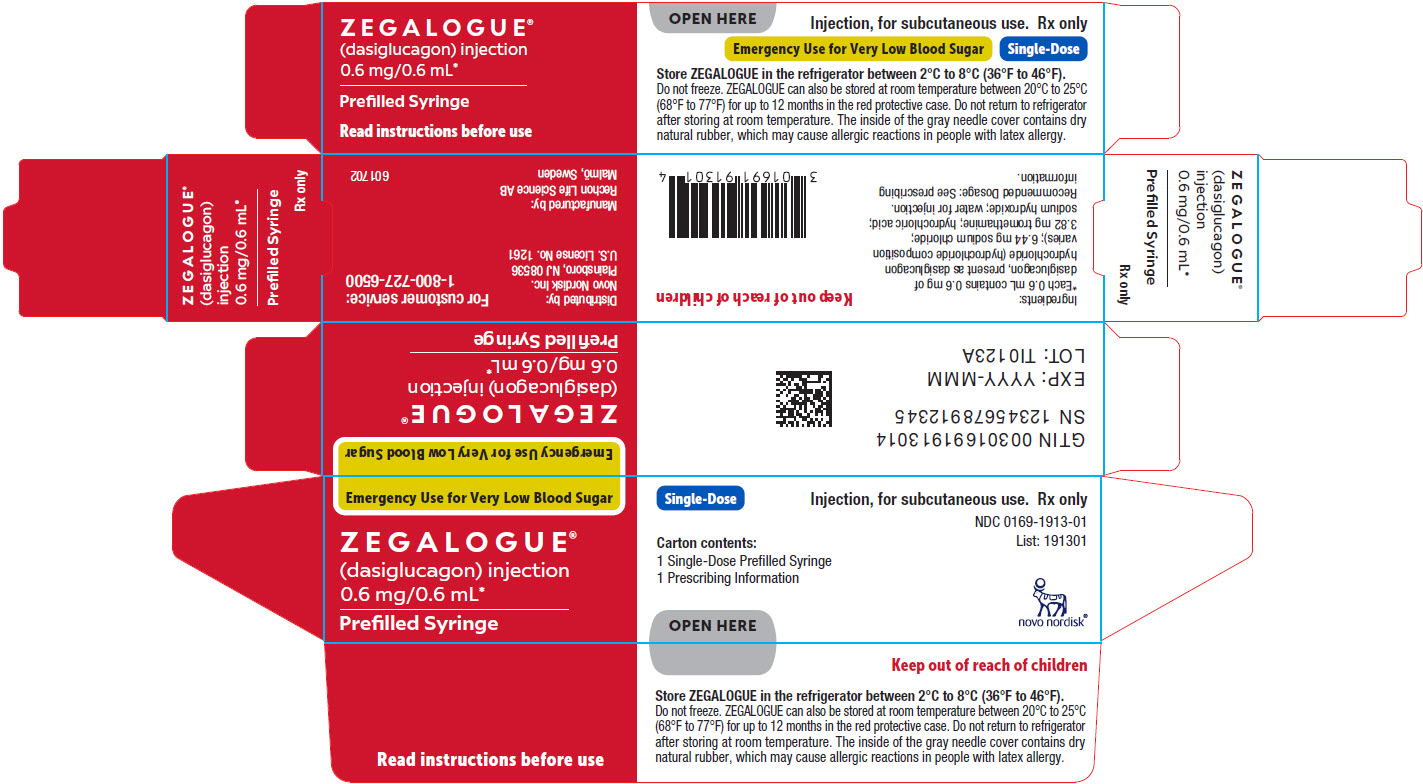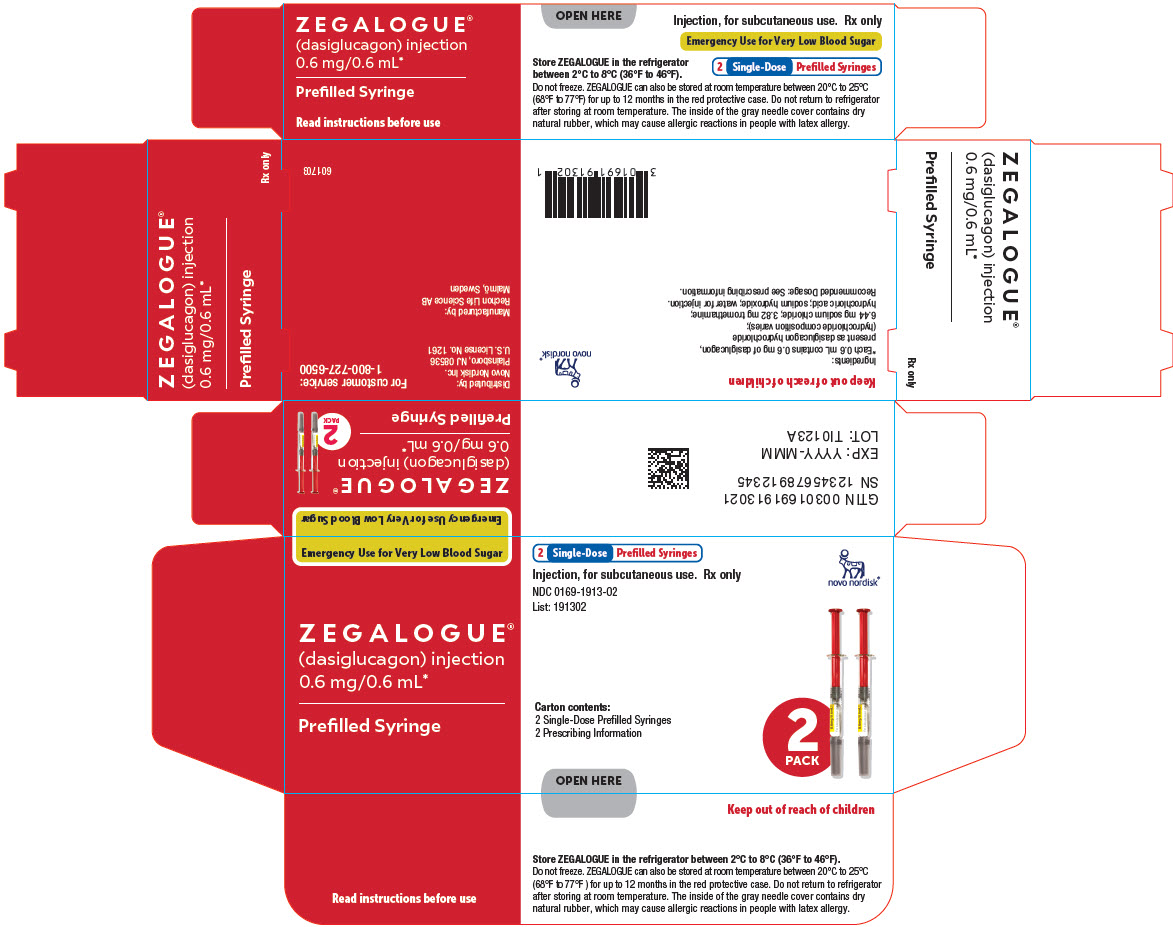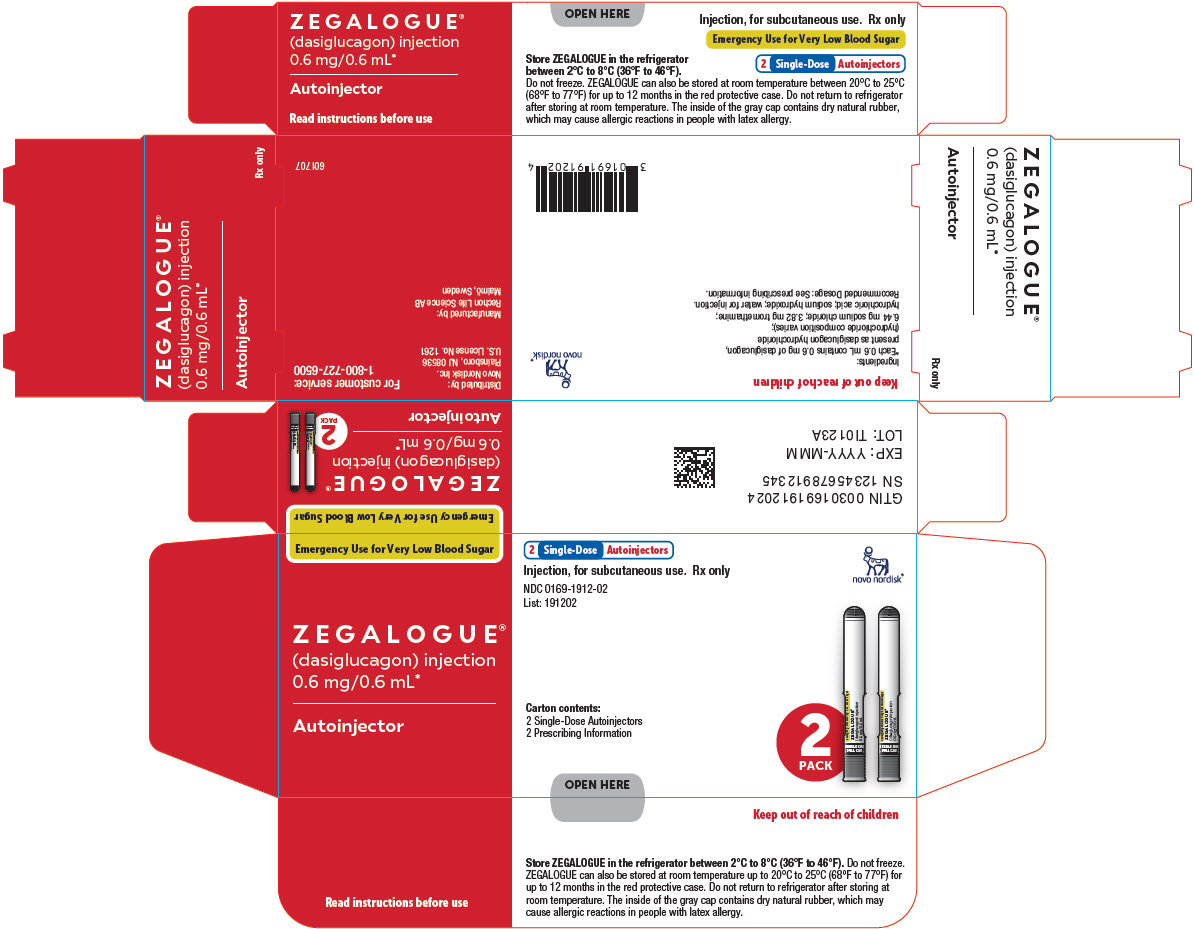 DRUG LABEL: Zegalogue
NDC: 0169-1913 | Form: INJECTION, SOLUTION
Manufacturer: Novo Nordisk
Category: prescription | Type: HUMAN PRESCRIPTION DRUG LABEL
Date: 20230101

ACTIVE INGREDIENTS: DASIGLUCAGON 0.6 mg/0.6 mL
INACTIVE INGREDIENTS: TROMETHAMINE 3.82 mg/0.6 mL; SODIUM CHLORIDE 6.44 mg/0.6 mL; WATER; HYDROCHLORIC ACID; SODIUM HYDROXIDE

HIGHLIGHTS OF PRESCRIBING INFORMATION

These highlights do not include all the information needed to use ZEGALOGUE® safely and effectively. See full prescribing information for ZEGALOGUE.
ZEGALOGUE (dasiglucagon) injection, for subcutaneous use
Initial U.S. Approval: 2021

1 INDICATIONS AND USAGE

ZEGALOGUE is an antihypoglycemic agent indicated for the treatment of severe hypoglycemia in pediatric and adult patients with diabetes aged 6 years and above. (1)

2 DOSAGE AND ADMINISTRATION

- ZEGALOGUE autoinjector and prefilled syringe are for subcutaneous injection only. (2.1)
- The dose in adults and pediatric patients aged 6 years and older is 0.6 mg. (2.2)
- Administer ZEGALOGUE according to the printed instructions on the protective case label and the Instructions For Use. (2.1)
- Visually inspect ZEGALOGUE prior to administration. The solution should appear clear, colorless, and free from particles. If the solution is discolored or contains particulate matter, do not use. (2.1)
- Administer the injection into the lower abdomen, buttocks, thigh, or outer upper arm. (2.1)
- Call for emergency assistance immediately after administering the dose. (2.1)
- If there has been no response after 15 minutes, an additional dose of ZEGALOGUE from a new device may be administered while waiting for emergency assistance. (2.1)
- When the patient has responded to treatment, give oral carbohydrates. (2.1)
- Do not attempt to reuse ZEGALOGUE. Each device contains a single dose of dasiglucagon and cannot be reused. (2.1)

3 DOSAGE FORMS AND STRENGTHS

Injection:

- 0.6 mg/0.6 mL single-dose autoinjector (3)
- 0.6 mg/0.6 mL single-dose prefilled syringe (3)

4 CONTRAINDICATIONS

Pheochromocytoma (4)

Insulinoma (4)

5 WARNINGS AND PRECAUTIONS

- Substantial Increase in Blood Pressure in Patients with Pheochromocytoma: Contraindicated in patients with pheochromocytoma because ZEGALOGUE may stimulate the release of catecholamines from the tumor. (4, 5.1)
- Hypoglycemia in Patients with Insulinoma: In patients with insulinoma, administration may produce an initial increase in blood glucose, but ZEGALOGUE may stimulate exaggerated insulin release from an insulinoma and cause subsequent hypoglycemia. If a patient develops symptoms of hypoglycemia after a dose of ZEGALOGUE, give glucose orally or intravenously. (4, 5.2)
- Hypersensitivity and Allergic Reactions: Allergic reactions have been reported with glucagon products and may include generalized rash, and in some cases anaphylactic shock with breathing difficulties and hypotension. (5.3)
- Lack of Efficacy in Patients with Decreased Hepatic Glycogen: ZEGALOGUE is effective in treating hypoglycemia only if sufficient hepatic glycogen is present. Patients in states of starvation, with adrenal insufficiency or chronic hypoglycemia may not have adequate levels of hepatic glycogen for ZEGALOGUE to be effective. Patients with these conditions should be treated with glucose. (5.4)

6 ADVERSE REACTIONS

Most common adverse reactions (≥2%) associated with ZEGALOGUE are:

Adults: nausea, vomiting, headache, diarrhea, and injection site pain

Pediatrics: nausea, vomiting, headache, and injection site pain (6.1)

To report SUSPECTED ADVERSE REACTIONS, contact Novo Nordisk Inc., at 1-800-727-6500 or FDA at 1-800-FDA-1088 or www.fda.gov/medwatch.

7 DRUG INTERACTIONS

- Beta-blockers: Patients taking beta-blockers may have a transient increase in pulse and blood pressure. (7)
- Indomethacin: In patients taking indomethacin, ZEGALOGUE may lose its ability to raise blood glucose or may produce hypoglycemia. (7)
- Warfarin: ZEGALOGUE may increase the anticoagulant effect of warfarin. (7)

FULL PRESCRIBING INFORMATION

1 INDICATIONS AND USAGE

ZEGALOGUE® is indicated for the treatment of severe hypoglycemia in pediatric and adult patients with diabetes aged 6 years and above.

2 DOSAGE AND ADMINISTRATION

2.1 Administration Instructions

ZEGALOGUE autoinjector and prefilled syringe are for subcutaneous injection only.

Instruct patients and their caregivers on the signs and symptoms of severe hypoglycemia. Because severe hypoglycemia requires the help of others to recover, instruct the patient to inform those around them about ZEGALOGUE and its Instructions For Use. Administer ZEGALOGUE as soon as possible when severe hypoglycemia is recognized.

Instruct the patient or caregiver to read the Instructions For Use at the time they receive a prescription for ZEGALOGUE. Emphasize the following instructions to the patient or caregiver:

- Administer ZEGALOGUE according to the printed instructions on the protective case label and the Instructions For Use.
- Visually inspect ZEGALOGUE prior to administration. The solution should appear clear, colorless, and free from particles. If the solution is discolored or contains particulate matter, do not use.
- Administer the injection in the lower abdomen, buttocks, thigh, or outer upper arm.
- Call for emergency assistance immediately after administering the dose.
- If there has been no response after 15 minutes, an additional dose of ZEGALOGUE may be administered while waiting for emergency assistance.
- When the patient has responded to treatment, give oral carbohydrates to restore liver glycogen and prevent recurrence of hypoglycemia.
- Do not attempt to reuse ZEGALOGUE. Each ZEGALOGUE device contains a single dose of dasiglucagon and cannot be reused.

2.2 Recommended Dosage

The recommended dose of ZEGALOGUE in adults and pediatric patients aged 6 years and older is 0.6 mg administered by subcutaneous injection into the lower abdomen, buttocks, thigh, or outer upper arm.

If there has been no response after 15 minutes, an additional 0.6 mg dose of ZEGALOGUE from a new device may be administered.

3 DOSAGE FORMS AND STRENGTHS

ZEGALOGUE injection is a clear, colorless solution available as:

- 0.6 mg/0.6 mL single-dose autoinjector
- 0.6 mg/0.6 mL single-dose prefilled syringe

4 CONTRAINDICATIONS

ZEGALOGUE is contraindicated in patients with:

- Pheochromocytoma because of the risk of substantial increase in blood pressure [see Warnings and Precautions (5.1)]
- Insulinoma because of the risk of hypoglycemia [see Warnings and Precautions (5.2)]

5 WARNINGS AND PRECAUTIONS

5.1 Substantial Increase in Blood Pressure in Patients with Pheochromocytoma

ZEGALOGUE is contraindicated in patients with pheochromocytoma because glucagon products may stimulate the release of catecholamines from the tumor [see Contraindications (4)]. If the patient develops a substantial increase in blood pressure and a previously undiagnosed pheochromocytoma is suspected, 5 to 10 mg of phentolamine mesylate, administered intravenously, has been shown to be effective in lowering blood pressure.

5.2 Hypoglycemia in Patients with Insulinoma

In patients with insulinoma, administration of glucagon products may produce an initial increase in blood glucose; however, ZEGALOGUE administration may directly or indirectly (through an initial rise in blood glucose) stimulate exaggerated insulin release from an insulinoma and cause hypoglycemia. ZEGALOGUE is contraindicated in patients with insulinoma [see Contraindications (4)]. If a patient develops symptoms of hypoglycemia after a dose of ZEGALOGUE, give glucose orally or intravenously.

5.3 Hypersensitivity and Allergic Reactions

Allergic reactions have been reported with glucagon products; these include generalized rash, and in some cases anaphylactic shock with breathing difficulties and hypotension. Advise patients to seek immediate medical attention if they experience any symptoms of serious hypersensitivity reactions.

5.4 Lack of Efficacy in Patients with Decreased Hepatic Glycogen

ZEGALOGUE is effective in treating hypoglycemia only if sufficient hepatic glycogen is present. Patients in states of starvation, with adrenal insufficiency or chronic hypoglycemia may not have adequate levels of hepatic glycogen for ZEGALOGUE administration to be effective. Patients with these conditions should be treated with glucose.

6 ADVERSE REACTIONS

The following important adverse reactions are described elsewhere in the labeling:

- Hypersensitivity and Allergic Reactions [see Warnings and Precautions (5.3)]

6.1 Clinical Trials Experience

Because clinical trials are conducted under widely varying conditions, adverse reaction rates observed in the clinical trials of ZEGALOGUE cannot be directly compared to rates in the clinical trials of another drug and may not reflect the rates observed in practice.

In clinical trials, 316 adult patients with type 1 diabetes and 20 pediatric patients with type 1 diabetes were exposed to ZEGALOGUE.

The data in Table 1 reflect exposure of 116 adult patients to ZEGALOGUE in 2 placebo-controlled trials (mean age 40 years). Table 2 reflects exposure of 20 pediatric patients exposed to ZEGALOGUE in a placebo-controlled trial. Eight patients were 7 to 11 years old, and 12 were 12 to 17 years old [see Clinical Studies (14)].

Table 1. Adverse Reactions Occurring ≥2% and More Frequently than with Placebo in ZEGALOGUE-treated Adult Patients within 12 hours of Treatment in 2 Placebo-Controlled Trials
Adverse reaction type | Placebo (N=53) | Dasiglucagon (N=116)
Adverse reaction type | % of Patients | % of Patients
Nausea | 4% | 57%
Vomiting | 2% | 25%
Headache | 4% | 11%
Diarrhea | 0% | 5%
Injection site pain | 0% | 2%

Table 2. Adverse Reactions Occurring ≥2% and More Frequently than with Placebo in ZEGALOGUE-treated Pediatric Patients within 12 hours of Treatment in a Placebo-Controlled Trial
Adverse reaction type | Placebo (N=11) | Dasiglucagon Age 6-11 years (N=8) | Dasiglucagon Age 12-17 years (N=12) | Dasiglucagon All (N=20)
 | % of Patients | % of Patients | % of Patients | % of Patients
Nausea | 0% | 25% | 92% | 65%
Vomiting | 0% | 25% | 67% | 50%
Headache | 0% | 0% | 17% | 10%
Injection site pain | 0% | 0% | 8% | 5%

Other Adverse Reactions

Other adverse reactions in patients treated with dasiglucagon occurring within 12 hours of treatment include: hypertension, hypotension, bradycardia, presyncope, palpitations, and orthostatic intolerance.

6.2 Immunogenicity

As with all therapeutic peptides, there is a potential for immunogenicity with ZEGALOGUE. The detection of antibody formation is highly dependent on the sensitivity and specificity of the assay. Additionally, the observed incidence of antibody (including neutralizing antibody) positivity in an assay may be influenced by several factors including assay methodology, sample handling, timing of sample collection, concomitant medications, and underlying disease. For these reasons, comparison of the incidence of antibodies to ZEGALOGUE with the incidence of antibodies to other products may be misleading.

In clinical trials, 4/498 (<1%) of ZEGALOGUE-treated patients developed treatment-emergent anti-drug antibodies (ADAs). Two patients receiving a single dose of ZEGALOGUE had detectable ADAs to dasiglucagon for at least 14 months after dosing. One ADA-positive patient receiving multiple doses of ZEGALOGUE had ADAs with transient neutralizing activity and with cross-reactivity against native glucagon. Although no safety or efficacy concerns were noted for these ADA-positive subjects, it is unknown whether ADAs may affect pharmacokinetics, pharmacodynamics, safety, and/or effectiveness of the drug [see Clinical Studies (14)].

7 DRUG INTERACTIONS

Table 3. Clinically Significant Drug Interactions with ZEGALOGUE
Beta-Blockers
Clinical Impact: | Patients taking beta-blockers may have a transient increase in pulse and blood pressure when given ZEGALOGUE.
Indomethacin
Clinical Impact: | In patients taking indomethacin, ZEGALOGUE may lose its ability to raise blood glucose or may even produce hypoglycemia.
Warfarin
Clinical Impact: | ZEGALOGUE may increase the anticoagulant effect of warfarin.

8 USE IN SPECIFIC POPULATIONS

8.1 Pregnancy

Risk Summary

There are no available data on dasiglucagon use in pregnant women to evaluate for a drug-associated risk of major birth defects, miscarriage or adverse maternal or fetal outcomes.

Untreated hypoglycemia in pregnancy can cause complications and may be fatal.

In animal reproduction studies, daily subcutaneous administration of dasiglucagon to pregnant rabbits and rats during the period of organogenesis did not cause adverse developmental effects at exposures 7 and 709 times the human dose of 0.6 mg based on AUC, respectively (see Data).

Data

Animal Data

In an embryo-fetal development study, pregnant rats were treated daily with subcutaneous doses of 2, 10, and 24 mg/kg/day during the period of organogenesis (gestation day 6 to 17). Maternal toxicity, in terms of decreased body weight gain, lower fetal body weight, and delayed bone ossification, was observed at ≥10 mg/kg/day (≥475 times the human dose, based on AUC).

In an embryo-fetal development study, pregnant rabbits were treated daily with subcutaneous doses of 0.1, 0.3, and 1 mg/kg/day during the period of organogenesis (gestation day 6 to 19). Lower fetal body weight and delayed bone ossification were observed at 1 mg/kg/day (100 times the human dose, based on AUC), a dose that also induced maternal toxicity in terms of decreased body weight gain. At ≥0.3 mg/kg/day (≥20 times the human dose), dasiglucagon caused fetal skeletal and visceral malformations. No adverse fetal developmental effects were observed at 0.1 mg/kg/day, corresponding to exposure 7 times the human dose.

8.2 Lactation

Risk Summary

There is no information on the presence of dasiglucagon in either human or animal milk, or the effects of the drug on the breastfed infant or milk production. Dasiglucagon is a peptide and would be expected to be broken down to its constituent amino acids in the infant's digestive tract and is therefore unlikely to cause harm to an exposed infant.

8.4 Pediatric Use

The safety and effectiveness of ZEGALOGUE for the treatment of severe hypoglycemia in patients with diabetes have been established in pediatric patients aged 6 years and above. Use of ZEGALOGUE for this indication is supported by evidence from a study in 42 pediatric patients with type 1 diabetes [see Clinical Studies (14.2)].

The safety and effectiveness of ZEGALOGUE have not been established in pediatric patients younger than 6 years of age.

8.5 Geriatric Use

Clinical studies of ZEGALOGUE included too few patients 65 years of age and older to determine whether these patients respond differently from younger adult patients.

10 OVERDOSAGE

If overdosage occurs, the patient may experience nausea, vomiting, inhibition of GI tract motility, and/or increases in blood pressure and heart rate. In case of suspected overdosing, serum potassium may decrease and should be monitored and corrected if needed. If the patient develops a marked increase in blood pressure, phentolamine mesylate has been shown to be effective in lowering blood pressure for the short time that control would be needed.

Appropriate supportive treatment should be initiated according to the patient's clinical signs and symptoms.

11 DESCRIPTION

ZEGALOGUE contains dasiglucagon hydrochloride, which is a glucagon analog and an antihypoglycemic agent. Dasiglucagon is comprised of 29 amino acids. The molecular formula of dasiglucagon (anhydrous, free-base) is C152H222N38O50, and its molecular mass is 3382 g/mol (anhydrous, free-base). Dasiglucagon hydrochloride has the following chemical structure:

ZEGALOGUE injection is a preservative free, sterile, aqueous, clear, and colorless solution for subcutaneous use in a single-dose prefilled syringe and an autoinjector. Each prefilled syringe and autoinjector contains 0.63 mg of dasiglucagon provided as dasiglucagon hydrochloride, which is a salt with 3 - 5 equivalents of hydrochloride, and contains the following inactive ingredients: 3.82 mg tromethamine, 6.44 mg sodium chloride, and water for injection. Hydrochloric acid and/or sodium hydroxide may have been added to adjust pH to 6.5.

12 CLINICAL PHARMACOLOGY

12.1 Mechanism of Action

Dasiglucagon is a glucagon receptor agonist, which increases blood glucose concentration by activating hepatic glucagon receptors, thereby stimulating glycogen breakdown and release of glucose from the liver. Hepatic stores of glycogen are necessary for dasiglucagon to produce an antihypoglycemic effect.

12.2 Pharmacodynamics

After administration of ZEGALOGUE in adult patients with type 1 diabetes, the mean glucose increase from baseline at 90 minutes was 168 mg/dL (Figure 1).

Figure 1. Mean plasma glucose over time in adults with type 1 diabetes administered 0.6 mg dasiglucagon

In pediatric patients (7 to 17 years) with type 1 diabetes, the mean glucose increase at 60 minutes after administration of ZEGALOGUE was 162 mg/dL (Figure 2).

Figure 2. Mean plasma glucose over time in pediatric patients with type 1 diabetes administered 0.6 mg dasiglucagon

Cardiac Electrophysiology

At a dose resulting in more than 5 times the concentration achieved with the recommended therapeutic dose, ZEGALOGUE does not prolong the QT interval to any clinically relevant extent.

12.3 Pharmacokinetics

Absorption

ZEGALOGUE absorption following subcutaneous injection of 0.6 mg resulted in a mean peak plasma concentration of 5110 pg/mL (1510 pmol/L) at around 35 minutes.

Distribution

The mean apparent volume of distribution was 47 L to 57 L following subcutaneous administration.

Elimination

The half-life was approximately 30 minutes.

Metabolism

Metabolism data indicated that dasiglucagon is cleared like native glucagon through proteolytic degradation pathways in blood, liver, and kidney.

Specific Populations

After administration of ZEGALOGUE in pediatric patients with type 1 diabetes, the mean peak plasma concentration of 3920 pg/mL occurred at around 21 minutes.

13 NONCLINICAL TOXICOLOGY

13.1 Carcinogenesis, Mutagenesis, Impairment of Fertility

Carcinogenesis

Long-term studies in animals to evaluate carcinogenicity of dasiglucagon have not been performed.

Mutagenesis

Dasiglucagon was not mutagenic or clastogenic in a standard battery of genotoxicity tests: bacterial mutagenicity (Ames), human lymphocyte chromosome aberration, and rat bone marrow micronucleus.

Impairment of Fertility

In a fertility and early embryofetal development study in rats, dasiglucagon administered by subcutaneous injection (0.5, 2, and 8 mg/kg/day) did not impair fertility in male and female rats at exposures 179 and 269 times the human dose of 0.6 mg (based on AUC), respectively.

14 CLINICAL STUDIES

Three randomized, double-blind, placebo-controlled, multicenter trials were conducted in patients with type 1 diabetes. Two trials (Trial A and Trial B) were conducted in adult patients, and one trial (Trial C) was conducted in pediatric patients aged 6 to 17 years. In all 3 trials, patients were randomized to ZEGALOGUE 0.6 mg, placebo, or (in Trials A and C) glucagon for injection 1.0 mg. ZEGALOGUE and the comparators were administered as single subcutaneous injections following a controlled induction of hypoglycemia using intravenous administration of insulin. During this procedure, a plasma glucose concentration of <60 mg/dL was targeted in Trials A and B, whereas the target was <80 mg/dL in Trial C.

The primary efficacy endpoint for all 3 trials was time to plasma glucose recovery (treatment success), defined as an increase in blood glucose of ≥20 mg/dL from time of administration, without additional intervention within 45 minutes. In Trials A and B, plasma glucose values were collected and assessed at pre-dose, and at 4, 6, 8, 10, 12, 15, 17, 20, 25, 30, 40, 45, 50, 60, 75, 90 minutes after treatment. Trial C assessed plasma glucose at the same timepoints as did Trials A and B, with the exception of the 25, 40, 50, 75 and 90-minute post-treatment timepoints. The primary hypothesis test was superiority of ZEGALOGUE versus placebo. There was no formal hypothesis test of ZEGALOGUE versus glucagon for injection.

14.1 Adult Patients

Trial A, NCT03378635: A total of 170 patients were randomized 2:1:1 to ZEGALOGUE, placebo, and glucagon for injection, stratified by injection sites (abdominal region, buttocks, thigh). The mean age of the patients was 39.1 years (96% were < 65 years), and the mean duration of diabetes was 20.0 years; 63% were male; 92% were White. The mean baseline plasma glucose was 58.8 mg/dL. The median time to plasma glucose recovery was statistically significantly shorter for ZEGALOGUE (10 minutes) versus placebo (40 minutes) (Table 4). Figure 3 shows the cumulative proportions of patients achieving plasma glucose recovery over time. The median time to plasma glucose recovery was numerically similar between ZEGALOGUE (10 minutes) and glucagon for injection (12 minutes).

Trial B, NCT03688711: A total of 45 patients were randomized 3:1 to ZEGALOGUE and placebo stratified by injection sites (buttocks, deltoid). The mean age of the patients was 41.0 years (95% were < 65 years), and the mean duration of diabetes was 22.5 years; 57% were male; 93% were White. The mean baseline plasma glucose was 55.0 mg/dL. The median time to plasma glucose recovery was statistically significantly shorter for ZEGALOGUE (10 minutes) versus placebo (35 minutes) (Table 4).

Table 4. Plasma Glucose Recovery in Adult Patients
 | Trial A |  | Trial B
 | ZEGALOGUE N=82 | Placebo N=43 | ZEGALOGUE N=34 | Placebo N=10
Median time to recovery [95% CI [log-log confidence interval] ] | 10 min [10; 10] [p < 0.001 versus placebo (log-rank test stratified by injection sites)] | 40 min [30; 40] | 10 min [8; 12] | 35 min [20; -)
N is the number of patients who were randomized and treated.

Figure 3 Time to plasma glucose recovery in Trial A

14.2 Pediatric Patients

Trial C, NCT03667053: Pediatric patients aged 6 to 17 years and weighing ≥20 kg, were randomized 2:1:1 to ZEGALOGUE, placebo, and glucagon for injection, stratified by injection sites (abdominal region, thigh) and age groups (6-11 years and 12-17 years). A total of 42 patients were randomized. The mean age was 12.5 years (range 7 to 17 years), and the mean duration of diabetes was 5.9 years; 56% were male; 95% were White. The mean baseline plasma glucose was 72.0 mg/dL. The median time to plasma glucose recovery was statistically significantly shorter for ZEGALOGUE (10 minutes) versus placebo (30 minutes) (Table 5). Figure 4 shows the cumulative proportions of pediatric patients achieving plasma glucose recovery over time. The median time to plasma glucose recovery was numerically similar between ZEGALOGUE (10 minutes) and glucagon for injection (10 minutes).

Table 5. Plasma Glucose Recovery in Pediatric Patients
 | Trial C
 | ZEGALOGUE N=20 | Placebo N=11
Median time to recovery [95% CI [log-log confidence interval] ] | 10 min [8; 12] [p < 0.001 versus placebo (log-rank test stratified by injection site and age group)] | 30 min [20; -)
N is the number of patients who were randomized and treated.

Figure 4. Time to plasma glucose recovery in Trial C

16 HOW SUPPLIED/STORAGE AND HANDLING

16.1 How Supplied

ZEGALOGUE injection is a clear, colorless solution supplied as follows:

Presentation | Strength | Package Size | NDC
Single-dose autoinjector | 0.6 mg/0.6 mL | 1 | 0169-1912-01
Single-dose autoinjector | 0.6 mg/0.6 mL | 2 | 0169-1912-02
Single-dose prefilled syringe | 0.6 mg/0.6 mL | 1 | 0169-1913-01
Single-dose prefilled syringe | 0.6 mg/0.6 mL | 2 | 0169-1913-02

16.2 Recommended Storage

Store ZEGALOGUE in a refrigerator, 2°C to 8°C (36°F to 46°F). Keep away from the cooling element. Do not freeze.

ZEGALOGUE can be kept at room temperature between 20°C to 25°C (68°F to 77°F) for up to 12 months. Record the date when the product was removed from the refrigerator in the space provided on the protective case. Do not return the product to the refrigerator after storing at room temperature. Store in the provided protective case and protect from light.

Discard ZEGALOGUE after the end of the 12-month period at room temperature storage, or after the expiration date stated on the product, whichever occurs first.

The inside of the gray cap on ZEGALOGUE autoinjector contains dry natural rubber (a derivative of latex).

The inside of the gray needle cover on ZEGALOGUE prefilled syringe contains dry natural rubber (a derivative of latex).

17 PATIENT COUNSELING INFORMATION

Advise the patient and family members or caregivers to read the FDA-approved patient labeling (Patient Information and Instructions For Use).

Recognition of Severe Hypoglycemia

Inform patient and family members or caregivers on how to recognize the signs and symptoms of severe hypoglycemia and the risks of prolonged hypoglycemia.

Administration

Review the Patient Information and Instructions For Use with the patient and family members or caregivers.

Serious Hypersensitivity

Inform patients that allergic reactions can occur with glucagon products like ZEGALOGUE. Advise patients to seek immediate medical attention if they experience any symptoms of serious hypersensitivity reactions [see Warnings and Precautions (5.3)].

Distributed by:

Novo Nordisk Inc.

Plainsboro, NJ, USA

Manufactured by:

Rechon Life Science AB

Malmö, Sweden

Patient Information
ZEGALOGUE (ze' gah log)
(dasiglucagon) injection, for subcutaneous use

What is ZEGALOGUE?
ZEGALOGUE is a prescription medicine used to treat very low blood sugar (severe hypoglycemia) in people with diabetes aged 6 years and older.
It is not known if ZEGALOGUE is safe and effective in children under 6 years of age.

Do not use ZEGALOGUE if you:

- have a tumor called pheochromocytoma in the gland on top of your kidneys (adrenal gland).
- have a tumor called insulinoma in your pancreas.

Before using ZEGALOGUE, tell your healthcare provider about all of your medical conditions, including if you:

- have a tumor in your pancreas.
- are allergic to dasiglucagon or any other ingredients in ZEGALOGUE. See the end of this Patient Information for a complete list of ingredients in ZEGALOGUE.
- have not had food or water for a long time (prolonged fasting or starvation).
- have adrenal insufficiency.
- have low blood sugar that does not go away (chronic hypoglycemia).
- are pregnant or plan to become pregnant.
- are breastfeeding or plan to breastfeed. It is not known if ZEGALOGUE passes into your breast milk. You and your healthcare provider should decide if you can use ZEGALOGUE while breastfeeding.

Tell your healthcare provider about all the medicines you take, including prescription and over-the-counter medicines, vitamins, and herbal supplements.

How should I use ZEGALOGUE?

- Read the detailed Instructions For Use that come with ZEGALOGUE.
- Use ZEGALOGUE exactly how your healthcare provider tells you to use it.
- Make sure your caregiver knows where you keep your ZEGALOGUE and how to use ZEGALOGUE the right way before you need it.
- Your caregiver must act quickly. Having very low blood sugar for a period of time may be harmful.
- Your healthcare provider will tell you how and when to use ZEGALOGUE.
- After giving ZEGALOGUE, your caregiver should call for emergency medical help right away.
- Once you are able to safely consume food or drink, your caregiver should give you a fast-acting source of sugar (such as fruit juice) and a long-acting source of sugar (such as crackers with cheese or peanut butter).
- If you do not respond to treatment after 15 minutes, your caregiver may give you another dose, if available.
- Tell your healthcare provider each time you use ZEGALOGUE. Your healthcare provider may need to change the dose of your other diabetes medicines.

What are the possible side effects of ZEGALOGUE?
ZEGALOGUE may cause serious side effects, including:

- high blood pressure. ZEGALOGUE can cause high blood pressure in certain people with tumors in their adrenal glands.
- low blood sugar. ZEGALOGUE can cause certain people with tumors in their pancreas called insulinomas to have low blood sugar.
- serious allergic reaction. Call your healthcare provider or get medical help right away if you have a serious allergic reaction including: rash, difficulty breathing, or low blood pressure (hypotension).

The most common side effects of ZEGALOGUE include:

1. Adults
2. nausea
3. vomiting
4. headache
5. diarrhea
6. injection site pain

1. Children
2. nausea
3. vomiting
4. headache
5. injection site pain

These are not all of the possible side effects of ZEGALOGUE. Call your doctor for medical advice about side effects. You may report side effects to FDA at 1-800-FDA-1088.

How should I store ZEGALOGUE?

- Store ZEGALOGUE in a refrigerator between 36°F to 46°F (2°C to 8°C).
- Do not freeze ZEGALOGUE.
- ZEGALOGUE can also be stored at room temperature between 68°F to 77°F (20°C to 25°C) for up to 12 months. See example in the Instructions For Use for how to keep track of this 12-month period.
- Do not return ZEGALOGUE to the refrigerator after storing at room temperature.
- Throw away ZEGALOGUE if it has been stored at room temperature for more than 12 months.
- Replace ZEGALOGUE before the expiration date printed on the red protective case.
- Store ZEGALOGUE in the red protective case it comes in.

Keep ZEGALOGUE and all medicines out of the reach of children.

General information about the safe use of ZEGALOGUE.
Medicines are sometimes prescribed for purposes other than those listed in a Patient Information leaflet. Do not use ZEGALOGUE for a condition for which it was not prescribed. Do not give ZEGALOGUE to other people, even if they have the same symptoms that you have. It may harm them. You can ask your pharmacist or healthcare provider for information about ZEGALOGUE that is written for healthcare professionals.

What are the ingredients in ZEGALOGUE?
Active ingredient: dasiglucagon, provided as dasiglucagon hydrochloride
Inactive ingredients: tromethamine, sodium chloride and water for injection. Hydrochloric acid and/or sodium hydroxide may be added to adjust pH

Distributed by: Novo Nordisk Inc., Plainsboro, NJ, USA

Manufactured by: Rechon Life Science AB, Malmö, Sweden

For more information go to www.zegalogue.com or call 1-800-727-6500.

This Patient Information has been approved by the U.S. Food and Drug Administration. Revised: 01/2023

INSTRUCTIONS FOR USE

ZEGALOGUE® (ze' gah log)
(dasiglucagon) injection

0.6 mg/0.6 mL

Emergency Use for Very Low Blood Sugar
Single-Dose
Prefilled Syringe
Injection, for subcutaneous use

Important: ZEGALOGUE is used to treat very low blood sugar (severe hypoglycemia) where you need help from others.

ZEGALOGUE contains 1 dose of dasiglucagon in a prefilled syringe and cannot be reused.

Read and understand this Instructions For Use before an emergency happens.

Show your family and friends where you keep ZEGALOGUE and explain how to use it by sharing these instructions, so they know how to use ZEGALOGUE before an emergency happens.

The inside of the gray needle cover contains dry natural rubber, which may cause allergic reactions in people with latex allergy.

Read before Injecting ZEGALOGUE

- Do not use ZEGALOGUE if the:
  - expiration date has passed
  - gray needle cover is missing or
  - syringe appears damaged
- When opening the red protective case make sure to hold it up straight (with the gray cap on top) to avoid dropping ZEGALOGUE.
- Do not remove the gray needle cover until you are ready to inject ZEGALOGUE.
- For questions or more information about ZEGALOGUE, call your healthcare provider.

Storage information

- Store ZEGALOGUE in the refrigerator between 36°F to 46°F (2°C to 8°C).
- Do not freeze.
- Store ZEGALOGUE in the red protective case it comes in.
- ZEGALOGUE can also be stored at room temperature between 68°F to 77°F (20°C to 25°C) for up to 12 months. See example to the right for how to keep track of this 12-month period.
- Do not return to refrigerator after storing at room temperature.
- Throw away ZEGALOGUE if it has been stored at room temperature for more than 12 months.
- Replace ZEGALOGUE before the expiration date printed on the red protective case.
- Keep ZEGALOGUE and all medicines out of the reach of children.

Description of parts

Before injection
Choose injection site and expose skin Injection sites include:; - Outer upper arms - Lower abdomen (at least 2 inches from the belly button) - Front or back of thighs - Buttocks; Roll back any clothing to expose bare skin. Do not inject through clothes. | Hold the red protective case upright and remove gray cap; - Hold the red protective case upright with the gray cap on top. - Pull the gray cap up to open. - Carefully remove ZEGALOGUE from the red protective case without dropping it.

How to inject

Step 1

Remove the gray needle cover

Pull the gray needle cover straight off. Be careful not to bend the needle.

Step 2

Pinch the skin and insert the needle

Gently pinch the skin and insert the entire needle into the skin at a 45° angle.

Step 3

Give the injection

After inserting the needle, release the pinched skin and slowly press the plunger rod all the way down until the syringe is empty and the plunger rod stops.

Step 4

Remove the needle

After the plunger rod stops and the injection is complete, carefully remove the needle from the injection site.

After injection

- After you have given the injection, roll the unconscious person on to their side to prevent choking.
- Call for emergency medical help or a healthcare provider right away after you have injected ZEGALOGUE. Even if the ZEGALOGUE injection helps the person to wake up, still call for emergency medical help right away. If the person does not respond after 15 minutes, another dose may be given, if available.
- Once the person is able to safely consume food or drink, give the person a fast-acting source of sugar (such as fruit juice) and a long-acting source of sugar (such as crackers with cheese or peanut butter).
- Replace the used ZEGALOGUE right away so you will have a new ZEGALOGUE in case you need it.

Hypoglycemia may happen again after receiving ZEGALOGUE treatment.

Early symptoms of hypoglycemia may include:

- sweating
- drowsiness
- dizziness
- sleep disturbances
- irregular heartbeat (palpitation)
- anxiety
- tremor
- blurred vision
- hunger
- slurred speech

- restlessness
- depressed mood
- tingling in the hands, feet, lips, or tongue
- irritability
- abnormal behavior
- lightheadedness
- unsteady movement
- inability to concentrate
- personality changes
- headache

If not treated early, hypoglycemia may worsen and the person may have severe hypoglycemia. Signs of severe hypoglycemia include confusion, seizures, unconsciousness, and death.

How to throw away (dispose of) ZEGALOGUE
Dispose of your ZEGALOGUE and the gray needle cover in an FDA-cleared sharps disposal container. | Put your expired or used needles and syringes in an FDA-cleared sharps disposal container right away after use. Do not throw away (dispose of) loose needles and syringes in your household trash.; If you do not have an FDA-cleared sharps disposal container, you may use a household container that is:; - made of a heavy-duty plastic - can be closed with a tight-fitting, puncture-resistant lid, without sharps being able to come out - upright and stable during use - leak-resistant - properly labeled to warn of hazardous waste inside the container; When your sharps disposal container is almost full, you will need to follow your community guidelines for the correct way to dispose of your sharps disposal container. There may be state or local laws about how you should throw away used syringes. For more information about safe sharps disposal, and for specific information about sharps disposal in the state that you live in, go to the FDA's website at: http://www.fda.gov/safesharpsdisposal; Do not dispose of your used sharps disposal container in your household trash unless your community guidelines permit it.; Do not recycle your used sharps disposal container.

This Instructions For Use has been approved by the U.S. Food and Drug Administration.

Distributed by:

Novo Nordisk Inc., Plainsboro, NJ, USA

Manufactured by:

Rechon Life Science AB, Malmö, Sweden

Revised 01/2023

INSTRUCTIONS FOR USE

ZEGALOGUE® (ze' gah log)

(dasiglucagon) injection

0.6 mg/0.6 mL

Emergency Use for Very Low Blood Sugar

Single-Dose

Autoinjector

Injection, for subcutaneous use

Important: ZEGALOGUE is used to treat very low blood sugar (severe hypoglycemia) where you need help from others.

ZEGALOGUE contains 1 dose of dasiglucagon in a prefilled autoinjector and cannot be reused.

Read and understand this Instructions For Use before an emergency happens.

Show your family and friends where you keep ZEGALOGUE and explain how to use it by sharing these instructions, so they know how to use ZEGALOGUE before an emergency happens.

The inside of the gray cap contains dry natural rubber, which may cause allergic reactions in people with latex allergy.

Read before injecting ZEGALOGUE

- Do not use ZEGALOGUE if the:
  - expiration date has passed
  - gray cap is missing or
  - autoinjector appears damaged
- When opening the red protective case make sure to hold it up straight (with the gray lid on top) to avoid dropping ZEGALOGUE.
- Do not remove the gray cap until you are ready to inject ZEGALOGUE.
- For questions or more information about ZEGALOGUE, call your healthcare provider.

Storage information

- Store ZEGALOGUE in the refrigerator between 36°F to 46°F (2°C to 8°C).
- Do not freeze.
- Store ZEGALOGUE in the red protective case it comes in.
- ZEGALOGUE can also be stored at room temperature between 68°F to 77°F (20°C to 25°C) for up to 12 months. See example to the right for how to keep track of this 12-month period.
- Do not return to refrigerator after storing at room temperature.
- Throw away ZEGALOGUE if it has been stored at room temperature for more than 12 months.
- Replace ZEGALOGUE before the expiration date printed on the red protective case.
- Keep ZEGALOGUE and all medicines out of the reach of children.

Description of parts

Before injection
Choose injection site and expose skin Injection sites include:; - Outer upper arms - Lower abdomen (at least 2 inches from the belly button) - Front or back of thighs - Buttocks; Roll back any clothing to expose bare skin. Do not inject through clothes. | Hold the red protective case upright and remove gray lid; - Hold the red protective case upright with the gray lid on top. - Pull the gray lid up to open. - Carefully remove ZEGALOGUE from the red protective case without dropping it.

How to inject

Step 1

Remove the gray cap from needle end

Pull the gray cap straight off.

Do not put your hand or fingers anywhere near the yellow needle guard. Touching the yellow needle guard may cause an accidental needle stick injury.

Step 2

Push and hold down ZEGALOGUE for 10 seconds and check window is red

Push ZEGALOGUE straight down on skin until the yellow needle guard is fully pressed down. You may hear the first click.

Keep holding ZEGALOGUE down and slowly count to 10 seconds. During this time the medicine window will turn red and you may hear a second click.

Check that the medicine window is red, which means that the full dose has been given.

Step 3
Remove ZEGALOGUE from injection site

Remove ZEGALOGUE by lifting it straight up.

The yellow needle guard will cover the needle and lock, preventing an accidental needle stick injury.

After injection

- After you have given the injection, roll the unconscious person on to their side to prevent choking.
- Call for emergency medical help or a healthcare provider right away after you have injected ZEGALOGUE. Even if the ZEGALOGUE injection helps the person to wake up, still call for emergency medical help right away. If the person does not respond after 15 minutes, another dose may be given, if available.
- Once the person is able to safely consume food or drink, give the person a fast-acting source of sugar (such as fruit juice) and a long-acting source of sugar (such as crackers with cheese or peanut butter).
- Replace the used ZEGALOGUE right away so you will have a new ZEGALOGUE in case you need it.

Hypoglycemia may happen again after receiving ZEGALOGUE treatment.

Early symptoms of hypoglycemia may include:

- sweating
- drowsiness
- dizziness
- sleep disturbances
- irregular heartbeat (palpitation)
- anxiety
- tremor
- blurred vision
- hunger
- slurred speech

- restlessness
- depressed mood
- tingling in the hands, feet, lips, or tongue
- irritability
- abnormal behavior
- lightheadedness
- unsteady movement
- inability to concentrate
- personality changes
- headache

If not treated early, hypoglycemia may worsen and the person may have severe hypoglycemia. Signs of severe hypoglycemia include confusion, seizures, unconsciousness, and death.

How to throw away (dispose of) ZEGALOGUE
Dispose of your ZEGALOGUE and gray cap in an FDA-cleared sharps disposal container. | Put your expired or used ZEGALOGUE in an FDA-cleared sharps disposal container right away after use. Do not throw away (dispose of) autoinjectors, loose needles and syringes in your household trash.; If you do not have an FDA-cleared sharps disposal container, you may use a household container that is:; - made of a heavy-duty plastic - can be closed with a tight-fitting, puncture-resistant lid, without sharps being able to come out - upright and stable during use - leak-resistant - properly labeled to warn of hazardous waste inside the container; When your sharps disposal container is almost full, you will need to follow your community guidelines for the correct way to dispose of your sharps disposal container. There may be state or local laws about how you should throw away used autoinjectors. For more information about safe sharps disposal, and for specific information about sharps disposal in the state that you live in, go to the FDA's website at: http://www.fda.gov/safesharpsdisposal; Do not dispose of your used sharps disposal container in your household trash unless your community guidelines permit it.; Do not recycle your used sharps disposal container.

This Instructions For Use has been approved by the U.S. Food and Drug Administration.

Distributed by:

Novo Nordisk Inc., Plainsboro, NJ, USA

Manufactured by:

Rechon Life Science AB, Malmö, Sweden

Revised 01/2023

PRINCIPAL DISPLAY PANEL - 0.6 mg/0.6 mL Prefilled Syringe 1ct Carton

Emergency Use for Very Low Blood Sugar

ZEGALOGUE®

(dasiglucagon) injection

0.6 mg/0.6 mL*

Prefilled Syringe

Single-Dose

Injection, for subcutaneous use. Rx only

NDC 0169-1913-01

List: 191301

Carton contents:

1 Single-Dose Prefilled Syringe

1 Prescribing Information

OPEN HERE

Novo Nordisk®

PRINCIPAL DISPLAY PANEL - 0.6 mg/0.6 mL Prefilled Syringe 2ct Carton

Emergency Use for Very Low Blood Sugar

ZEGALOGUE®

(dasiglucagon) injection

0.6 mg/0.6 mL*

Prefilled Syringe

2 Single-Dose Prefilled Syringes

Injection, for subcutaneous use. Rx only Novo Nordisk ®

NDC 0169-1913-02

List: 191302

Carton contents:

2 Single-Dose Prefilled Syringes

2 Prescribing Information

OPEN HERE 2 PACK

Package/Label Display Panel - 0.6 mg/0.6 mL 1ct Autoinjector Carton

Emergency Use for Very Low Blood Sugar

ZEGALOGUE®

(dasiglucagon) injection

0.6 mg/0.6 mL*

Autoinjector

Single-Dose Injection, for subcutaneous use. Rx only

NDC 0169-1912-01

List: 191201

Carton contents:

1 Single-Dose Autoinjector

1 Prescribing Information

OPEN HERE Novo Nordisk ®

Package/Label Display Panel - 0.6 mg/0.6 mL 2ct Autoinjector Carton

Emergency Use for Very Low Blood Sugar

ZEGALOGUE®

(dasiglucagon) injection

0.6 mg/0.6 mL*

Autoinjector

2 Single-Dose Autoinjectors

Injection, for subcutaneous use. Rx only Novo Nordisk ®

NDC 0169-1912-02

List: 191202

Carton contents:

2 Single-Dose Autoinjectors

2 Prescribing Information

OPEN HERE 2 PACK